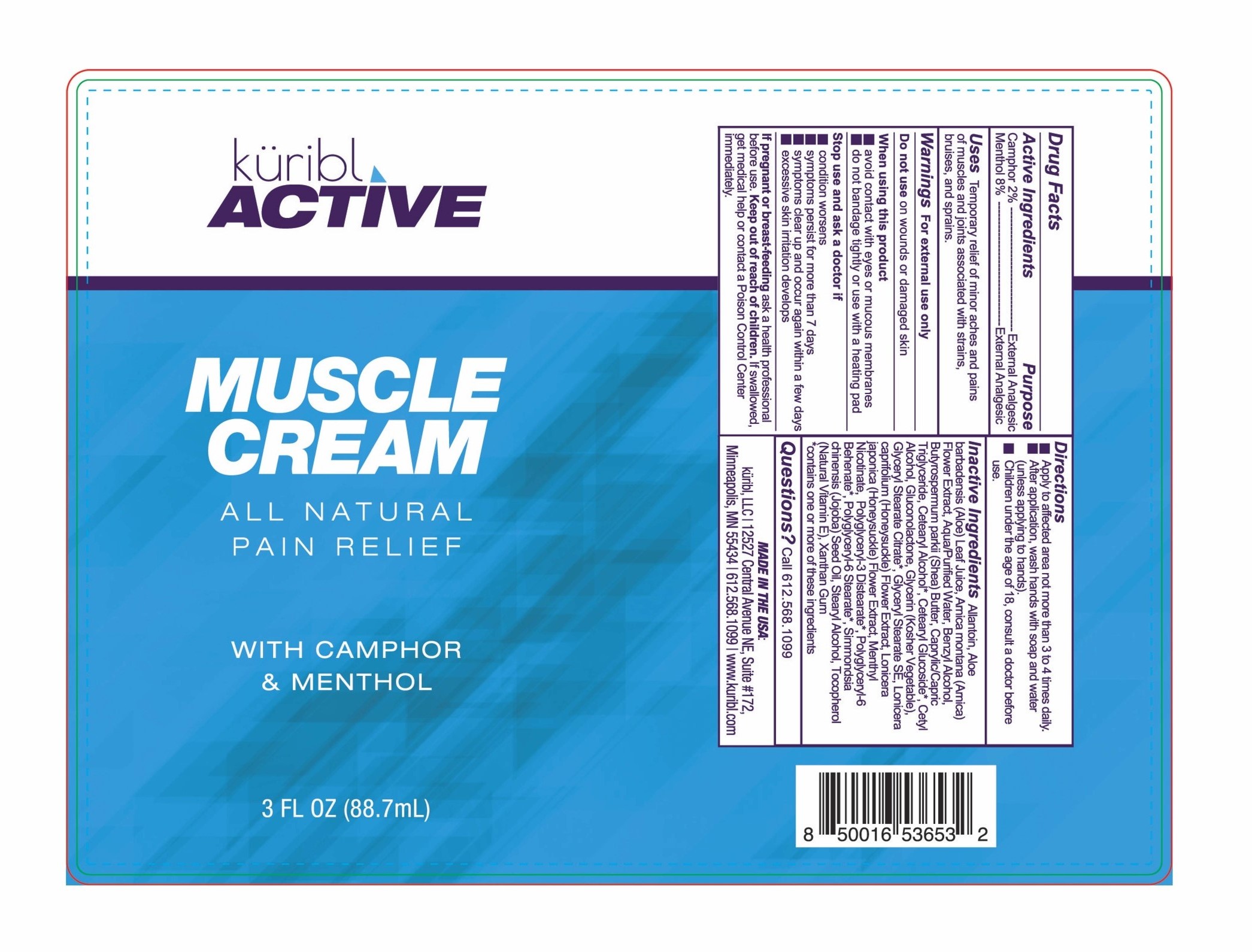 DRUG LABEL: Kuribl Active Muscle
NDC: 83111-003 | Form: CREAM
Manufacturer: Radiance Beauty & Wellness Inc. dba Saavy Naturals
Category: otc | Type: HUMAN OTC DRUG LABEL
Date: 20230223

ACTIVE INGREDIENTS: CAMPHOR (NATURAL) 2 g/100 mL; MENTHOL 8 g/100 mL
INACTIVE INGREDIENTS: ALOE VERA LEAF; ALLANTOIN; BENZYL ALCOHOL; POLYGLYCERYL-3 DISTEARATE; ARNICA MONTANA FLOWER; MEDIUM-CHAIN TRIGLYCERIDES; CETOSTEARYL ALCOHOL; STEARYL ALCOHOL; XANTHAN GUM; CETYL ALCOHOL; GLYCERYL STEARATE SE; JOJOBA OIL; GLUCONOLACTONE; GLYCERIN; GLYCERYL STEARATE CITRATE; LONICERA JAPONICA FLOWER; SHEA BUTTER; CETEARYL GLUCOSIDE; WATER; LONICERA CAPRIFOLIUM FLOWER; TOCOPHEROL; POLYGLYCERYL-6 BEHENATE; POLYGLYCERYL-6 STEARATE

Kuribl Active Muscle Cream

Active ingredients Purpose

Camphor 2% External Analgesics

Menthol 8% External Analgesics

Uses

Temporary relief of minor aches and pains of muscles and joints associated with strains, bruises, and sprains

Keep out of reach of children. If swallowed, get medical help or contact a Poison Control Center.

Stop use and ask a doctor if

- condition worsens
- symptoms persist for more than 7 days
- symptoms clear up and occur again within a few days
- excessive skin irritation develops

Warnings For external use only

Do not use on wounds or damaged skin

When using this product

- avoid contact with eyes or mucous membranes
- do not bandage tightly or use with heating pad

If pregnant or breast-feeding ask a health professional before use

Directions

- Apply to affected area not more than 3 to 4 times daily
- After application, wash hands with soaps and water (unless applying to hands).
- Children under the age of 18, consult a doctor before use

INACTIVE INGREDIENT

Inactive Ingredients Allantoin, Aloe Barbadensis (Aloe) Leaf Juice, Arnica Montana (Arnica) Flower Extract, Aqua/Purified, Benzyl Alcohol, Butyrospermum parkii (Shea) Butter, Caprylic/Capric Triglyceride, Cetearyl Alcohol, Cetearyl Glucoside, Cetyl Alcohol, Gluconolactone, Glycerin (Kosher Vegetable), Glyceryl Stearate Citrate, Glyceryl Stearate SE, Lonicera Caprifolium (Honeysuckle) Flower Extract, Lonicera Japonica (Honeysuckle) Flower Extract, Menthyl Nicotinate, Polyglyceryl-3 Distearate, Polyglyceryl-6 Behenate, Polyglyceryl-6 Stearate, Simmondia chinensis (Jojoba) Seed Oil, Stearyl Alcohol, Tocopherol (Natural Vitamin E), Xanthan Gum

PACKAGE LABEL

kuribl Active

Muscle Cream

All Natural Pain Relief with Camphor & Menthol

3 FL OZ (88.7 mL)